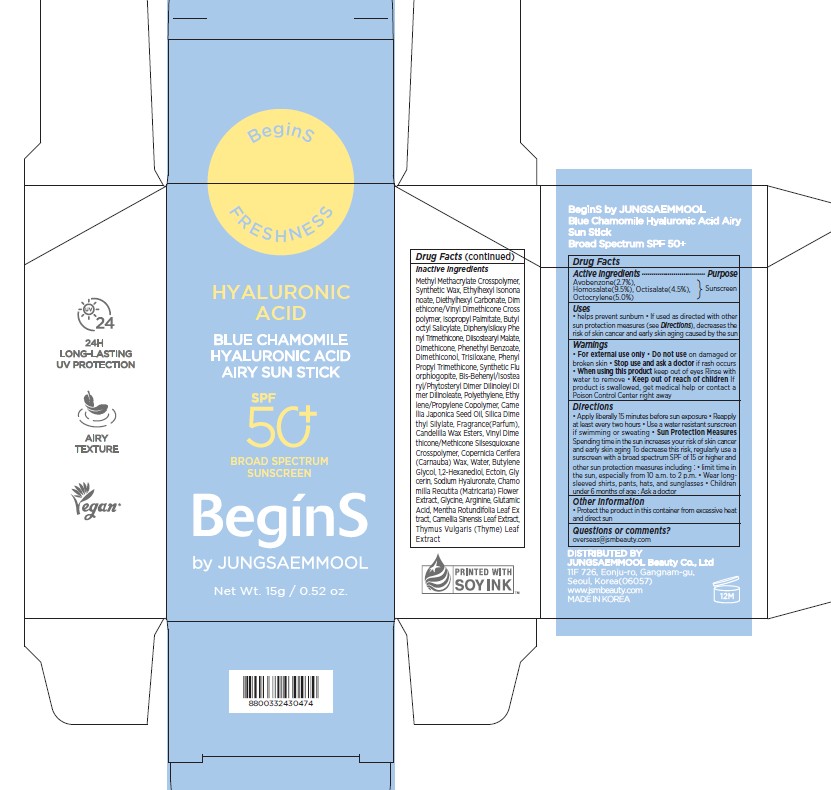 DRUG LABEL: BeginS by JUNGSAEMMOOL Blue Chamomile Hyaluronic Acid Airy Sun Stick Broad Spectrum SPF 50 plus
NDC: 71261-041 | Form: CREAM
Manufacturer: Jungsaemmool Beauty Co., Ltd.
Category: otc | Type: HUMAN OTC DRUG LABEL
Date: 20260124

ACTIVE INGREDIENTS: AVOBENZONE 27 mg/1 g; HOMOSALATE 95 mg/1 g; OCTISALATE 45 mg/1 g; OCTOCRYLENE 50 mg/1 g
INACTIVE INGREDIENTS: ETHYLHEXYL ISONONANOATE; DIETHYLHEXYL CARBONATE; DIMETHICONE/VINYL DIMETHICONE CROSSPOLYMER (HARD PARTICLE); ISOPROPYL PALMITATE; BUTYLOCTYL SALICYLATE; DIPHENYLSILOXY PHENYL TRIMETHICONE; DIISOSTEARYL MALATE; DIMETHICONE, UNSPECIFIED; PHENETHYL BENZOATE; TRISILOXANE; PHENYL PROPYL TRIMETHICONE; MAGNESIUM POTASSIUM ALUMINOSILICATE FLUORIDE; BIS-BEHENYL/ISOSTEARYL/PHYTOSTERYL DIMER DILINOLEYL DIMER DILINOLEATE; HIGH DENSITY POLYETHYLENE; CAMELLIA JAPONICA SEED OIL; SILICA DIMETHYL SILYLATE; VINYL DIMETHICONE/METHICONE SILSESQUIOXANE CROSSPOLYMER; CARNAUBA WAX; LIMONENE, (+)-; .BETA.-CITRONELLOL, (R)-; LINALOOL, (+/-)-; GERANIOL; WATER; BUTYLENE GLYCOL; 1,2-HEXANEDIOL; ECTOINE; GLYCERIN; HYALURONATE SODIUM; CHAMOMILE; GLYCINE; ARGININE; GLUTAMIC ACID; MENTHA X ROTUNDIFOLIA LEAF; GREEN TEA LEAF; THYMUS VULGARIS LEAF

71261-041_BeginS by JUNGSAEMMOOL Blue Chamomile Hyaluronic Acid Airy Sun Stick Broad Spectrum SPF 50 plus

KEEP OUT OF REACH OF CHILDREN

Keep out of reach of the children. If product is swallowed, get medical help or contact a poison control center right away.

ACTIVE INGREDIENT

Avobenzone 2.7%

Homosalate 9.5%

Octisalate 4.5%

Octocrylene 5.0%

PURPOSE

Sunscreen

INDICATIONS AND USAGE

helps prevent sunburn

If used as directed with other sun protection measures (see Directions), decreases the risk of skin cancer and early skin aging caused by the sun

WARNINGS

For external use only

Do not use on damaged or broken skin

When using this product, keep out of eyes. Rinse with water to remove.

Stop using and ask a doctor if rash occurs.

DOSAGE AND ADMINISTRATION

Apply liberally 15 minutes before sun exposure. Reapply at least every two hours

Use a water resistant sunscreen if swimming or sweating

Sun protection measures. Spending time in the sun increases your risk of skin cancer and early skin aging. To decrease this risk, regularly use a sunscreen with a broad spectrum SPF of 15 or higher and other sun protection measures including: - Limit time in the sun, especially from 10 am to 2 pm. - Wear long-sleeve shirts, pants, hats, and sunglasses

Children under 6 months of age: Ask a doctor

INACTIVE INGREDIENT

Methyl Methacrylate Crosspolymer, Synthetic Wax, Ethylhexyl Isononanoate, Diethylhexyl Carbonate, Dimethicone/Vinyl Dimethicone Crosspolymer, Isopropyl Palmitate, Butyloctyl Salicylate, Diphenylsiloxy Phenyl Trimethicone, Diisostearyl Malate, Dimethicone, Phenethyl Benzoate, Dimethiconol, Trisiloxane, Phenyl Propyl Trimethicone, Synthetic Fluorphlogopite, Bis-Behenyl/Isostearyl/Phytosteryl Dimer Dilinoleyl Dimer Dilinoleate, Polyethylene, Ethylene/Propylene Copolymer, Camellia Japonica Seed Oil, Silica Dimethyl Silylate, Fragrance(Parfum), Candelilla Wax Esters, Vinyl Dimethicone/Methicone Silsesquioxane Crosspolymer, Copernicia Cerifera (Carnauba) Wax, Limonene, Citronellol, Linalool, Geraniol, Water, Butylene Glycol, 1,2-Hexanediol, Ectoin, Glycerin, Sodium Hyaluronate, Chamomilla Recutita (Matricaria) Flower Extract, Glycine, Arginine, Glutamic Acid, Mentha Rotundifolia Leaf Extract, Camellia Sinensis Leaf Extract, Thymus Vulgaris (Thyme) Leaf Extract

OTHER SAFETY INFORMATION

Protect the product in the container from excessive heat and direct sun